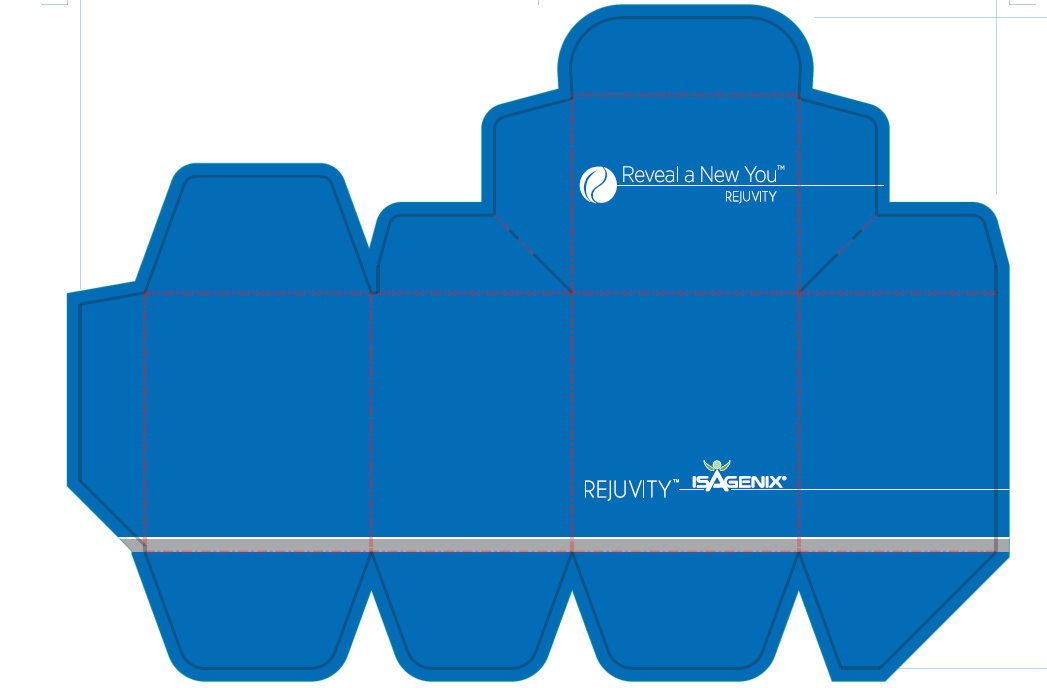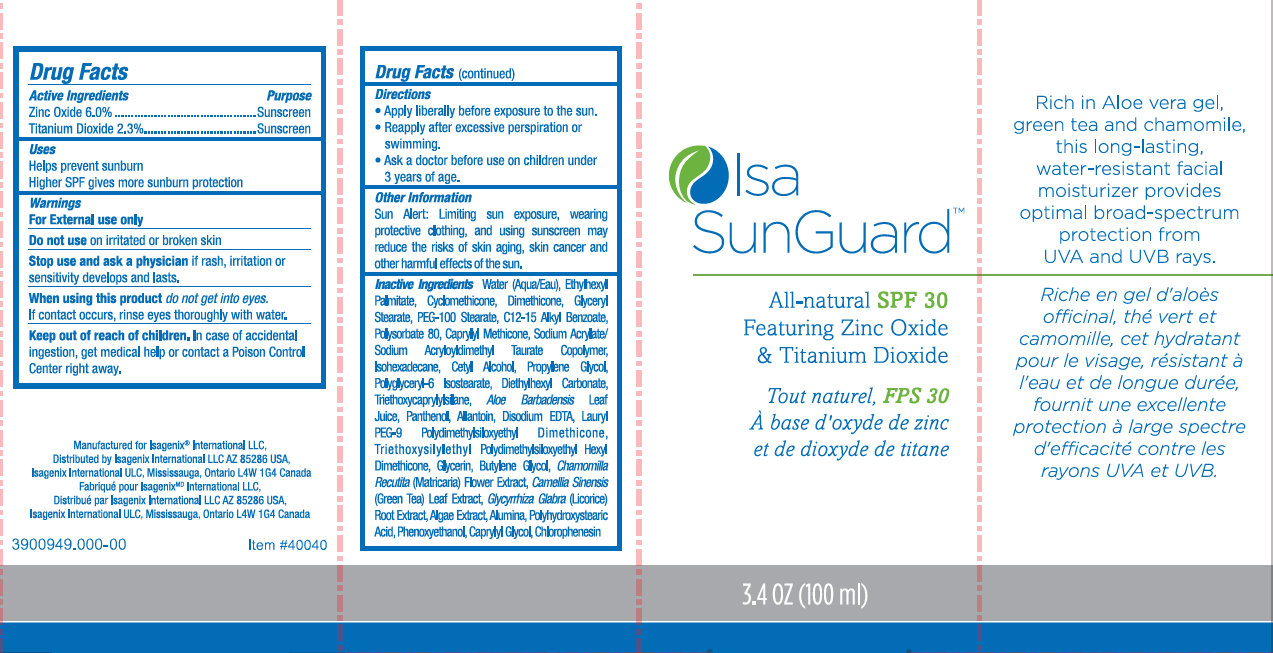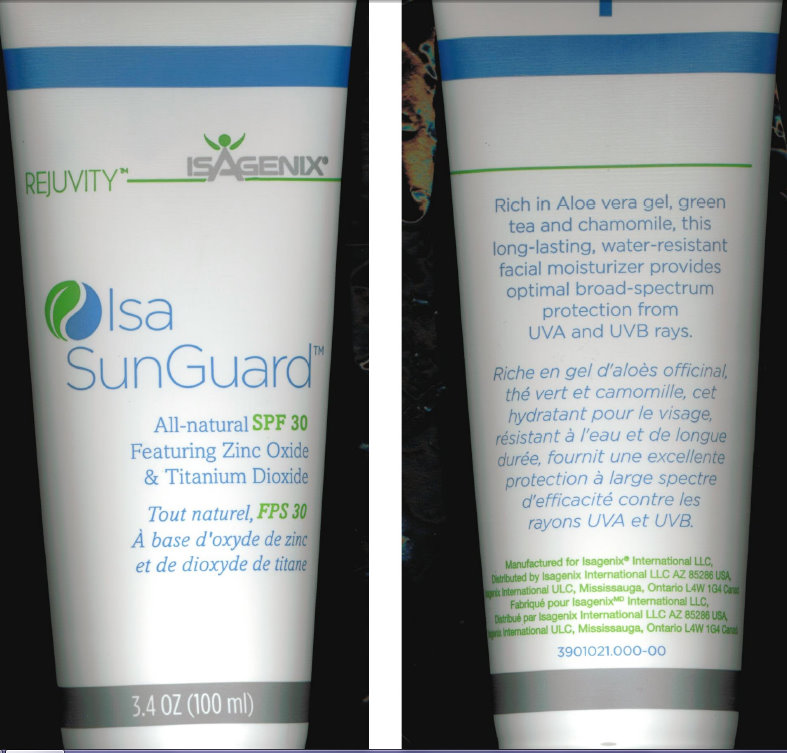 DRUG LABEL: Isa SunGuard SPF 30
NDC: 76187-850 | Form: CREAM
Manufacturer: Isagenix International, LLC
Category: otc | Type: HUMAN OTC DRUG LABEL
Date: 20231212

ACTIVE INGREDIENTS: ZINC OXIDE 60 mg/1 mL; TITANIUM DIOXIDE 23 mg/1 mL
INACTIVE INGREDIENTS: WATER; ETHYLHEXYL PALMITATE; CYCLOMETHICONE; DIMETHICONE; GLYCERYL MONOSTEARATE; PEG-100 STEARATE; ALKYL (C12-15) BENZOATE; POLYSORBATE 80; ISOHEXADECANE; CETYL ALCOHOL; PROPYLENE GLYCOL; DIETHYLHEXYL CARBONATE; TRIETHOXYCAPRYLYLSILANE; ALOE VERA LEAF; PANTHENOL; ALLANTOIN; EDETATE DISODIUM; GLYCERIN; BUTYLENE GLYCOL; CHAMOMILE; GREEN TEA LEAF; GLYCYRRHIZA GLABRA; ALUMINUM OXIDE; POLYHYDROXYSTEARIC ACID (2300 MW); PHENOXYETHANOL; CAPRYLYL GLYCOL

Isa SunGuard SPF 30

ACTIVE INGREDIENT

Active Ingredients Purpose Zinc Oxide 6.0%.......................................Sunscreen Titanium Dioxide 2.3%..............................Sunscreen

PURPOSE

Uses Helps prevent sunburn Higher SPF gives more sunburn protection

Uses

Helps prevent sunburn

Higher SPF gives more sunburn protection

Warnings For External use only

Do not use on irritated or broken skin

Stop use and ask a physician if rash, irritation or sensitivity develops and lasts.

When using this product do not ger into eyes. If contact occurs, rinse eyes thoroughly with water.

Keep out of reach of children.

OTHER SAFETY INFORMATION

In case of accidental ingestion, get medical help or contact a Poison Control Center right away.

DOSAGE AND ADMINISTRATION

Directions - Apply liberally before sun exposure to the sun. - Reapply after excessive perspiration or swimming. - Ask a doctor before use on children under 3 years of age.

Other information Sun alert: Limiting sun exposure, wearing protective clothing, and using sunscreen may reduce the risk of skin aging, skin cancer, and other harmful effects of the sun.

INACTIVE INGREDIENT

Inactive Ingredients Water (Aqua/Eau), Ethylhexyl Palmitate, Cyclomethicone, Dimethicone, Glyceryl Stearate, PEG-100 Stearate, C12-15 Alkyl Benzoate, Polysorbate 80, Caprylyl Methicone, Sodium Acrylate/ Sodium Acryloyldimethyl Taurate Copolymer, Isohexadecane, Cetyl Alcohol, Propylene Glycol, Polyglyceryl-6 Isostearate, Diethylhexyl Carbonate, Triethoxycaprylylsilane, Aloe Barbadensis Leaf Juice, Panthenol, Allantoin, Disodium EDTA, Lauryl PEG-9 Polydimethylsiloxyethyl Dimethicone, Triethoxysilyllethyl Polydimethylsiloxyethyl Hexyl Dimethicone, Glycerin, Butylene Glycol, Chamomilla Recutita (Matricaria) Flower Extract, Camellia Sinensis (Green Tea) Leaf Extract, Glycyrrhiza Glabra (Licorice) Root Extract, Algae Extract, Alumina, Polyhydroxystearic Acid, Phenoxyethanol, Caprylyl Glycol, Chlorophenesin

DESCRIPTION

Rich in Aloe vera gel, green tea and chamomile, this long-lasting, water-resistant facial moisturizer provides optimal broad-spectrum protection from UVA and UVB rays. Manufactured for Isagenix International LLC, Distributed by Isagenix International LLC AZ 85286 USA. Isagenix International ULC, Mississauga, Ontario L4W 1G4 Canada 3900949.000-00 Item #40040

PACKAGE LABEL

Reveal a New You REJUVITY REJUVITY ISAGENIX

PACKAGE LABEL

Isa SunGuard All-natural SPF 30 Featuring Zinc Oxide and Titanium Dioxide 3.4 OZ (100 ml)

PACKAGE LABEL

REJUVITY ISAGENIX Isa SunGuard All-natural SPF 30 Featuring Zinc Oxide and Titanium Dioxide 3.4 OZ (100 ml) Rich in Aloe vera gel, green tea and chamomile, this long-lasting, water-resistant facial moisturizer provides optimal broad-spectrum protection from UVA and UVB rays. Manufactured for Isagenix International LLC, Distributed by Isagenix International LLC AZ 85286 USA. Isagenix International ULC, Mississauga, Ontario L4W 1G4 Canada 3901021.000-00